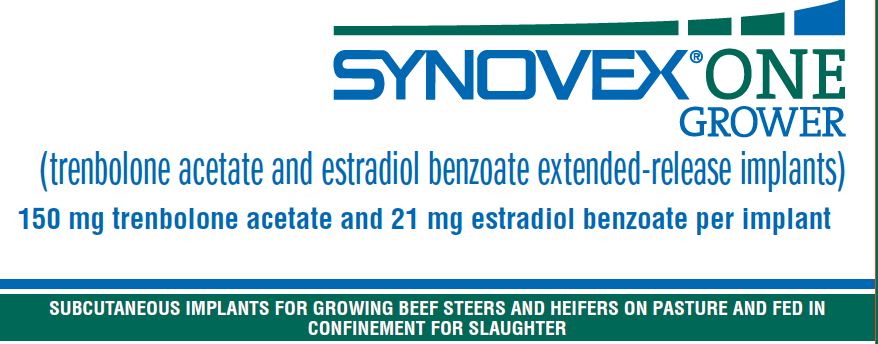 DRUG LABEL: Synovex One
NDC: 54771-2012 | Form: IMPLANT
Manufacturer: Zoetis Inc.
Category: animal | Type: OTC ANIMAL DRUG LABEL
Date: 20211109

ACTIVE INGREDIENTS: TRENBOLONE ACETATE 150 mg/1 1; ESTRADIOL BENZOATE 21 mg/1 1

SYNOVEX® ONE GROWER

SYNOVEX® ONE GROWER
(trenbolone acetate and estradiol benzoate extended-release implants)
150 mg trenbolone acetate and 21 mg estradiol benzoate per implant

SUBCUTANEOUS IMPLANTS FOR GROWING BEEF STEERS AND HEIFERS ON PASTURE AND FED IN CONFINEMENT FOR SLAUGHTER

Description

SYNOVEX ONE Grower (trenbolone acetate and estradiol benzoate extended-release implants) is a growth promoting implant containing 150 mg of trenbolone acetate and 21 mg of estradiol benzoate per implant with a porous polymer film coating that extends the pay-out period of the final formulation up to 200 days. Each implant consists of six pellets. Ten implants are provided in each cartridge.

DOSAGE

One implant (six pellets), containing 150 mg of trenbolone acetate and 21 mg of estradiol benzoate, is administered to each steer or heifer by subcutaneous implantation in the middle one‑third of the ear.
The ten-dose cartridge of SYNOVEX ONE Grass is designed to be used exclusively with a Synovex Applicator.

WITHDRAWAL PERIODS AND RESIDUE WARNINGS

No withdrawal period is required when used according to labeling.
Do not use in beef calves less than 2 months of age, dairy calves, and veal calves. A withdrawal period has not been established for this product in pre-ruminating calves.
Do not use in dairy cows or in animals intended for subsequent breeding. Use in these cattle may cause drug residues in milk and/or in calves born to these cows.
Implant pellets subcutaneously in ear only. Any other location is a violation of Federal law. Do not attempt salvage of implanted site for human or animal food.

USER SAFETY WARNINGS

Not for use in humans. Keep out of reach of children.

ANIMAL SAFETY WARNING

Bulling has occasionally been reported in implanted steers and heifers. Vaginal and rectal prolapse, udder development, ventral edema and elevated tailheads have occasionally been reported in heifers administered SYNOVEX ONE Grower implants.

DIRECTIONS

Each cartridge cell holds one implant (6 pellets), containing 150 mg trenbolone acetate and 21 mg of estradiol benzoate.
Administer complete contents of one cartridge cell (one implant) to each steer or heifer by subcutaneous implantation in the middle one-third of the ear.
The ten-dose cartridge of SYNOVEX ONE Grower is designed to be used exclusively with a Synovex® applicator. Approved implantation technique is fully described in the fold-out carton section. Never sacrifice careful, clean technique for speed of implantation.

STORAGE

Store unopened product at controlled room temperature 20°-25°C (68°-77°F) with excursions between 15°-30°C (59°-86°F). Avoid excessive heat and humidity.
Use product before the expiration date on the label.
Once the pouch is opened, unused product may be stored in the end-folded pouch (away from light) for up to six months under refrigerated conditions 2°-8°C (36°-47°F) or at room temperature 20°-25°C (68°-77°F) with excursions between 15°-30°C (59°-86°F) for up to one month.

DISPOSAL

SYNOVEX ONE Grower waste materials should be disposed of according to prescribed Federal, State, and Local guidelines.

INDICATIONS FOR USE

- For increased rate of weight gain for up to 200 days in growing beef steers and heifers on pasture (stocker, feeder and slaughter).
- For increased rate of weight gain for up to 200 days in growing beef steers and heifers fed in confinement for slaughter.
- Not approved for repeated implantation (reimplantation) with this or any other cattle ear implant within each separate production phase:
  - growing beef steers and heifers on pasture (stocker, feeder and slaughter);
  - growing beef steers and heifers fed in confinement for slaughter.
- Safety and effectiveness following reimplantation have not been evaluated

Do not use in beef calves less than 2 months of age, dairy calves, and veal calves because effectiveness and safety have not been established.
Do not use in animals intended for subsequent breeding, or in dairy cows.
NOTE: The administration of SYNOVEX ONE Grower may result in decreased marbling scores when compared to non-implanted steers and heifers.

NET CONTENTS

NET CONTENTS: 10 CARTRIDGES
Each Cartridge Contains 10 implants (100 implants total)

Manufactured By A Non-Sterilizing Process
Restricted Drug (California)—
Use Only As Directed.
IMPORTANT:
Read ALL sides of carton
Approved by FDA under NADA # 141-348
zoetis
Distributed by:
Zoetis Inc.
Kalamazoo, MI 49007
40034339

PRINCIPAL DISPLAY PANEL - 10 Cartridge Implant Carton

40034339